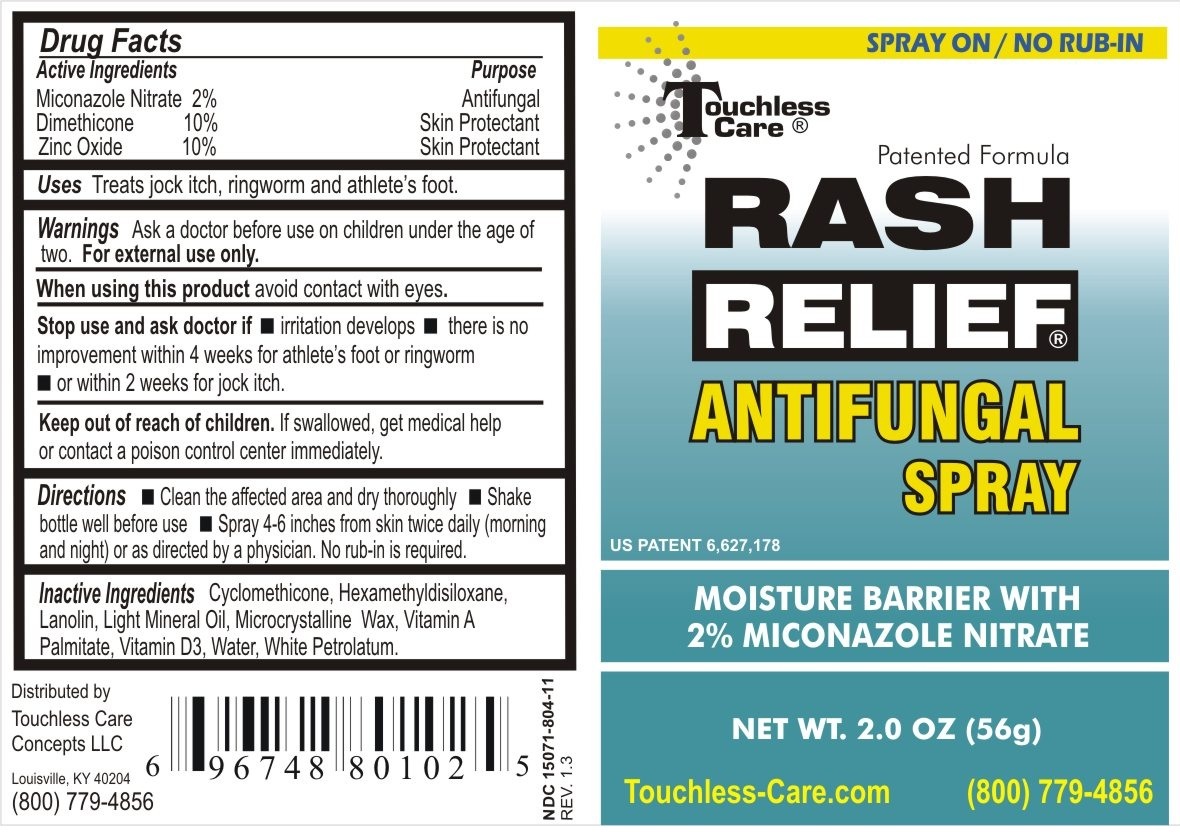 DRUG LABEL: Rash Relief Antifungal
NDC: 15071-804 | Form: LIQUID
Manufacturer: Touchless Care Concepts LLC
Category: otc | Type: HUMAN OTC DRUG LABEL
Date: 20111116

ACTIVE INGREDIENTS: Miconazole Nitrate 2 g/100 g; Dimethicone 10 g/100 g; Zinc Oxide 10 g/100 g
INACTIVE INGREDIENTS: Mineral Oil; Cyclomethicone; Lanolin; Microcrystalline Wax; Hexamethyldisiloxane; Water; Cholecalciferol; Vitamin A Palmitate; Petrolatum

RASH RELIEF ANTIFUNGAL SPRAY

Active Ingredients

Miconazole Nitrate 2%

Dimethicone 10%

Petrolatum 10%

Purpose

Antifungal / Skin Protectant

Warnings

- Ask a doctor before use on children under the age of two. For external use only.

- When using this product do not get into eyes.

- Stop use and ask a doctor if: irritation develops; there is no improvement within 4 weeks for athlete's foot or ringworm; or within 2 weeks for jock itch.

Directions

- Clean the affected area and dry thoroughly.

- Shake bottle well before use.

- Spray 4-6 inches from skin twice daily (morning and night) or as directed by a physician. No rub-in is required.

Inactive Ingredients

Cyclomethicone, Hexamethyldisiloxane, Lanolin, Light Mineral Oil, Microcrystalline Wax, Vitamin A Palmitate, Vitamin D3, Water, White Petrolatum

INDICATIONS AND USAGE

Uses: Treats jock itch, ringworm, and athlete's foot

- Keep out of reach of children. If swallowed, get medical help or contact a local poison control center immediately